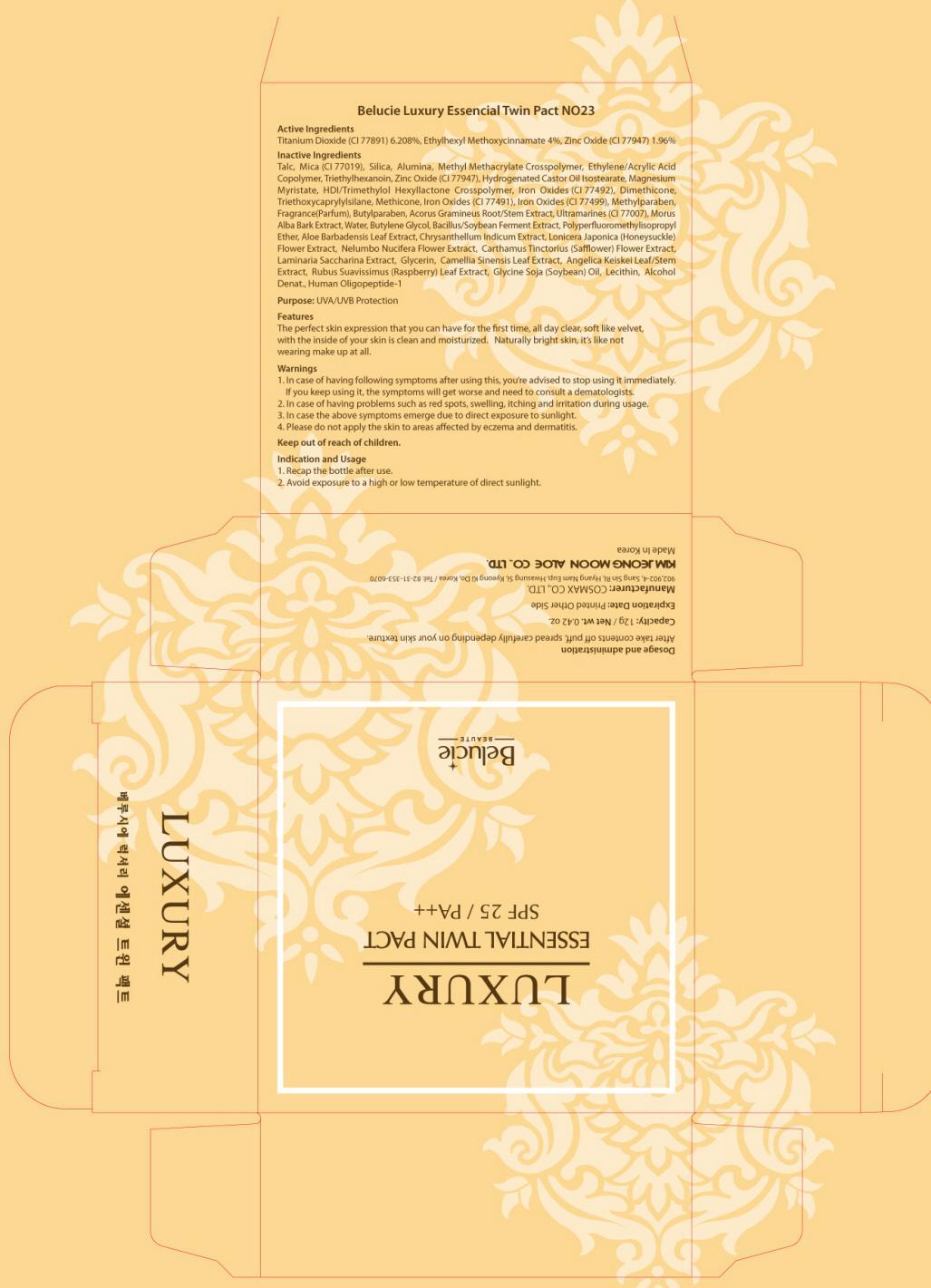 DRUG LABEL: Belucie Luxury Essential Twin Pact NO23
NDC: 50410-020 | Form: POWDER
Manufacturer: KIMJEONGMOON ALOE CO., LTD.
Category: otc | Type: HUMAN OTC DRUG LABEL
Date: 20121128

ACTIVE INGREDIENTS: Titanium Dioxide 0.744 g/12 g; OCTINOXATE 0.48 g/12 g; Zinc Oxide 0.235 g/12 g
INACTIVE INGREDIENTS: Talc; Mica; Triethylhexanoin

ACTIVE INGREDIENT

Active Ingredients: Titanium Dioxide 6.208%, Ethylhexyl Methoxycinnamate 4%, Zinc Oxide 1.96%

INACTIVE INGREDIENT

Inactive Ingredients: Talc, Mica (CI 77019), Silica, Alumina, Methyl Methacrylate Crosspolymer, Ethylene/Acrylic Acid Copolymer, Triethylhexanoin, Zinc Oxide (CI 77947), Hydrogenated Castor Oil Isostearate, Magnesium Myristate, HDI/Trimethylol Hexyllactone Crosspolymer, Iron Oxides (CI 77492), Dimethicone, Triethoxycaprylylsilane, Methicone Iron Oxides (CI 77491), Iron Oxides (CI 77499), Methylparaben, Fragrance(Parfum), Butylparaben, Acorus Gramineus Root/Stem Extract, Ultramarines (CI 77007), Morus Alba Bark Extract, Water, Butylene Glycol, Bacillus/Soybean Ferment Extract, Polyperfluoromethylisopropyl Ether, Aloe Barbadensis Leaf Extract, Chrysanthellum Indicum Extract, Lonicera Japonica (Honeysuckle) Flower Extract, Nelumbo Nucifera Flower Extract, Carthamus Tinctorius (Safflower) Flower Extract, Laminaria Saccharina Extract, Glycerin, Camellia Sinensis Leaf Extract, Angelica Keiskei Leaf/Stem Extract, Rubus Suavissimus (Raspberry) Leaf Extract, Glycine Soja (Soybean) Oil, Lecithin, Alcohol Denat., Human Oligopeptide-1

PURPOSE

Purpose: UVA/UVB Protection

WARNINGS

1. In case of having following symptoms after using this, you’re advised to stop using it immediately. If you keep using it, the symptoms will get worse and need to consult a dematologists.
2. In case of having problems such as red spots, swelling, itching and irritation during usage
3. In case the above symptoms emerge due to direct exposure to sunlight
4. Please do not apply the skin to areas affected by eczema and dermatitis

KEEP OUT OF REACH OF CHILDREN

INDICATIONS AND USAGE

Indication and usage
1. Recap the bottle after use.
2. Avoid exposure to a high or low temperature of direct sunlight

DOSAGE AND ADMINISTRATION

After take contents off puff, spread carefully depending on your skin texture.